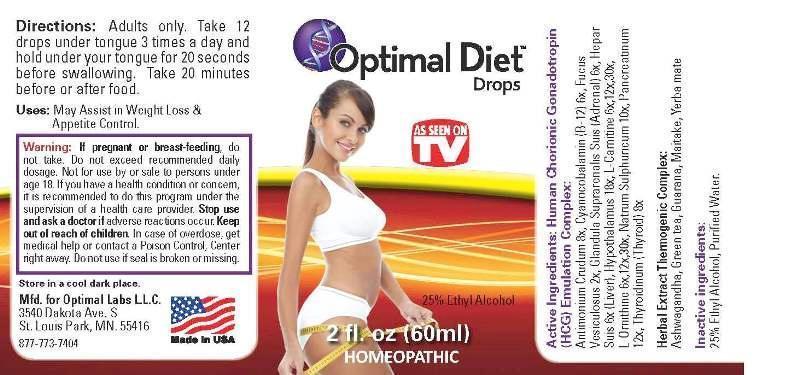 DRUG LABEL: Optimal Diet Drops
NDC: 49710-0001 | Form: LIQUID
Manufacturer: Optimal Labs LLC
Category: homeopathic | Type: HUMAN OTC DRUG LABEL
Date: 20130326

ACTIVE INGREDIENTS: FUCUS VESICULOSUS 2 [hp_X]/1 mL; CYANOCOBALAMIN 6 [hp_X]/1 mL; SUS SCROFA ADRENAL GLAND 6 [hp_X]/1 mL; PORK LIVER 6 [hp_X]/1 mL; LEVOCARNITINE 6 [hp_X]/1 mL; ORNITHINE 6 [hp_X]/1 mL; ANTIMONY TRISULFIDE 8 [hp_X]/1 mL; SUS SCROFA THYROID 8 [hp_X]/1 mL; SODIUM SULFATE 10 [hp_X]/1 mL; PANCRELIPASE 12 [hp_X]/1 mL; SUS SCROFA HYPOTHALAMUS 18 [hp_X]/1 mL
INACTIVE INGREDIENTS: GREEN TEA LEAF; MAITAKE; WITHANIA SOMNIFERA ROOT; PAULLINIA CUPANA SEED; ILEX PARAGUARIENSIS LEAF; WATER; ALCOHOL

Drug Facts

ACTIVE INGREDIENTS

Fucus Vesiculosus 2X, Cyanocobalamin 6X, Glandula Suprarenalis Suis 6X, Hepar Suis 6X, L Carnitine 6X, 12X, 30X, L Ornithine 6X, 12X, 30X, Antimonium Crudum 8X, Thyroidinum (Suis) 8X, Natrum Sulphuricum 10X, Pancreatinum 12X, Hypothalamus (Suis) 18X

INDICATIONS

May Assist in Weight Loss and Appetite Control.

WARNINGS

If pregnant or breast-feeding, do not take. Do not exceed recommended daily dosage. Not for use by or sale to persons under age 18. If you have a health condition or concern, it is recommended to do this program under the supervision of a health care provider. Stop use and ask a doctor if adverse reactions occur. Keep out of reach of children. In case of overdose get medical help or contact a Poison Control, Center right away. Do not use if seal is broken or missing.

DIRECTIONS

Adults only. Take 12 drops under tongue 3 times a day and hold under your tongue for 20 seconds before swallowing. Take 20 minutes before or after food.

INACTIVE INGREDIENTS

Green tea (leaf), Maitake (fruit), Ashwagandha (root), Guarana (seed), Mate (leaf), Water, Ethanol 25%

KEEP OUT OF REACH OF CHILDREN

In case of overdose get medical help or contact a Poison Control, Center right away.

INDICATIONS AND USAGE

May Assist in Weight Loss and Appetite Control.

QUESTIONS

Mfd. for Optimal Labs L.L.C.

3540 Dakota Ave. S.

St. Louis Park, MN 55416

877-773-7404

PACKAGE LABEL

Optimal Diet Drops

AS SEEN ON TV

2 fl. oz (60 ml)

HOMEOPATHIC